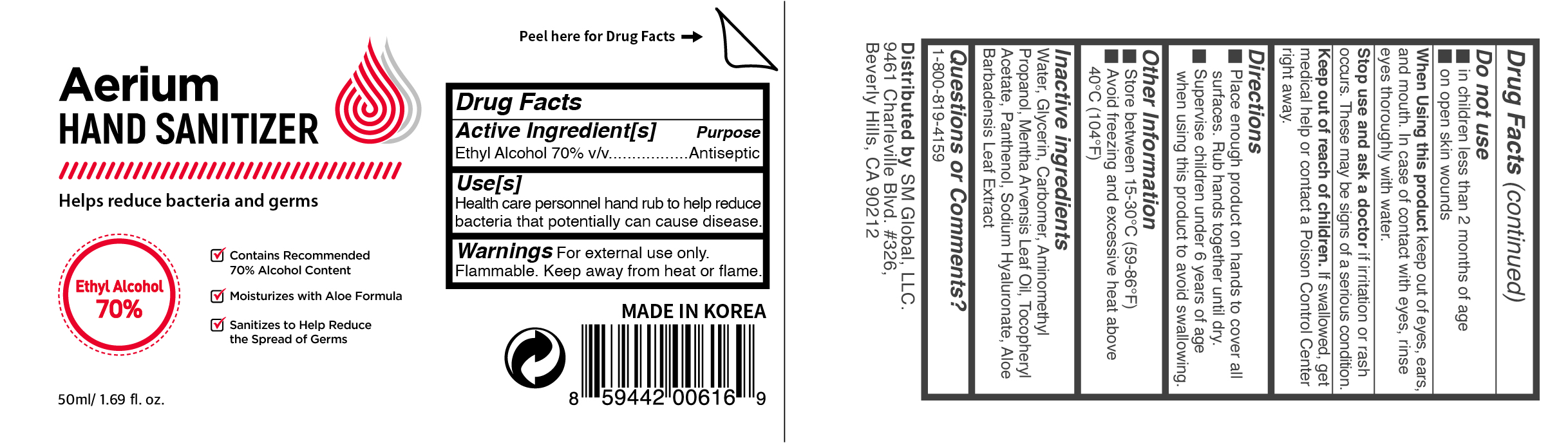 DRUG LABEL: Aerium Hand Sanitizer 70% 50ml
NDC: 74924-102 | Form: GEL
Manufacturer: SM Global, LLC.
Category: otc | Type: HUMAN OTC DRUG LABEL
Date: 20200525

ACTIVE INGREDIENTS: ALCOHOL 70 mL/100 mL
INACTIVE INGREDIENTS: MENTHA ARVENSIS LEAF OIL; ALOE VERA LEAF; GLYCERIN; AMINOMETHYLPROPANOL; WATER; CARBOMER 940; .ALPHA.-TOCOPHEROL ACETATE; PANTHENOL; HYALURONATE SODIUM

Aerium Hand Sanitizer 70% 50ml

Active Ingredient(s)

Ethyl Alcohol 70% v/v. Purpose: Antiseptic

Purpose

Antiseptic, Hand Sanitizer

Use

Health care personnel hand rub to help reduce bacteria that potentially can cause disease.

Warnings

For external use only. Flammable. Keep away from heat or flame

Do not use

- in children less than 2 months of age
- on open skin wounds

When using

When using this product keep out of eyes, ears, and mouth. In case of contact with eyes, rinse eyes thoroughly with water.

Stop use

Stop use and ask a doctor if irritation or rash occurs. These may be signs of a serious condition.

Keep out

Keep out of reach of children. If swallowed, get medical help or contact a Poison Control Center right away.

Directions

- Place enough product on hands to cover all surfaces. Rub hands together until dry.
- Supervise children under 6 years of age when using this product to avoid swallowing.

Other information

- Store between 15-30C (59-86F)
- Avoid freezing and excessive heat above 40C (104F)

Inactive ingredients

Water, Glycerin, Carbomer, Aminomethyl Propanol, Mentha Arvensis Leaf Oil, Tocopheryl Acetate, Panthenol, Sodium Hyaluronate, Aloe Barbadensis Leaf Extract

Questions or Comments?

1-800-819-4159

Package Label - Principal Display Panel

Aerium Hand Sanitizer
Helps reduce bacteria and germs

Contains Recommended 70 % Alcohol Content
Moisturizes with Aloe Formula
Sanitizes to Help Reduce the Spread of Germs

Ethyl Alcohol 70%

50ml / 1.69 fl.oz